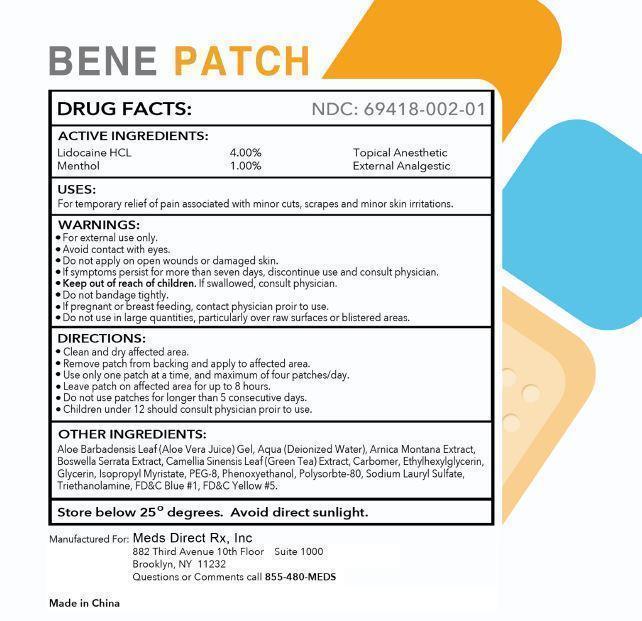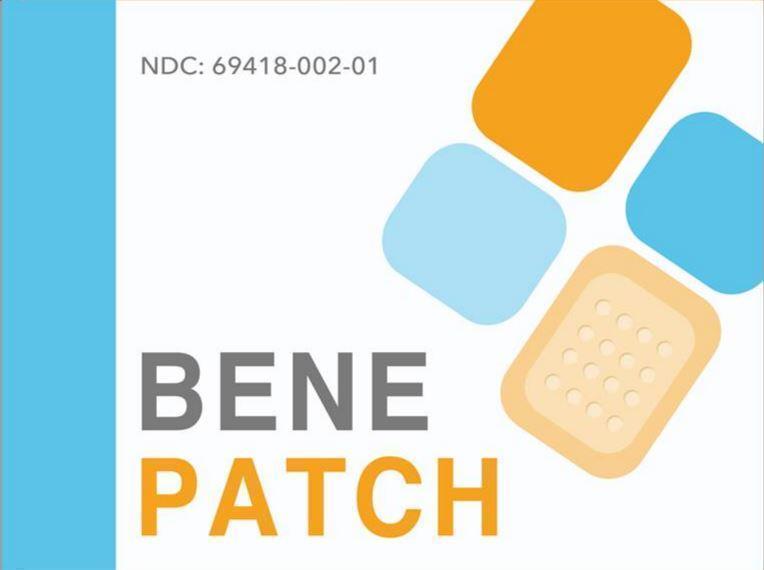 DRUG LABEL: BenePatch
NDC: 69418-002 | Form: PATCH
Manufacturer: Meds Direct Rx, Inc.
Category: otc | Type: HUMAN OTC DRUG LABEL
Date: 20151118

ACTIVE INGREDIENTS: MENTHOL 1 g/100 g; LIDOCAINE HYDROCHLORIDE 4 g/100 g
INACTIVE INGREDIENTS: FD&C BLUE NO. 1; GREEN TEA LEAF; GLYCERIN; PEG-8 STEARATE; ISOPROPYL MYRISTATE; PHENOXYETHANOL; ALOE VERA LEAF; POLYSORBATE 80; SODIUM LAURYL SULFATE; TROLAMINE; ARNICA MONTANA; INDIAN FRANKINCENSE; FD&C YELLOW NO. 5; ETHYLHEXYLGLYCERIN; CARBOMER HOMOPOLYMER TYPE C (ALLYL PENTAERYTHRITOL CROSSLINKED); WATER

BenePatch (69418-002)

ACTIVE INGREDIENTS:

Lidocaine HCL 4.00%
Menthol 1.00%

PURPOSE

Topical Anesthetic
External Analgesic

USES:

For temporary relieft of pain associated with minor cuts, scrapes and minor skin irritations.

WARNINGS:

- For external use only.
- Avoid contact with eyes.
- Do not apply on open wounds or damaged skin.
- If symptoms persist for more than seven days, discontinue use and consult physician.
- Do not bandage tightly.
- If pregnant or breast-feeding, contact physician prior to use.
- Do not use in large quantities, particularly over raw surfaces or blistered areas.

Keep out of reach of children.

If swallowed, consult physician.

DIRECTIONS:

- Clean and dry affected area.
- Remove patch from backing and apply to affected area.
- Use only one patch at a time, and maximum of four patches/day.
- Leave patch on affected area for up to 8 hours.
- Do not use patches for longer than 5 consecutive days.
- Children under 12 should consult physician prior to use.

OTHER INGREDIENTS:

Aloe Barbadensis Leaf (Aloe Vera Juice) Gel, Aqua (Deionized Water), Arnica Montana Extract, Boswellia Serrata Extract, Camellia Sinensis Leaf (Green Tea) Extract, Carbomer, Ethylhexylglycerin, Glycerin, Isopropyl Myristate, PEG-8, Phenoxyethanol, Polysorbate-80, Sodium Lauryl Sulfate, Triethanolamine, FD&C Blue #1, FD&C Yellow #5.